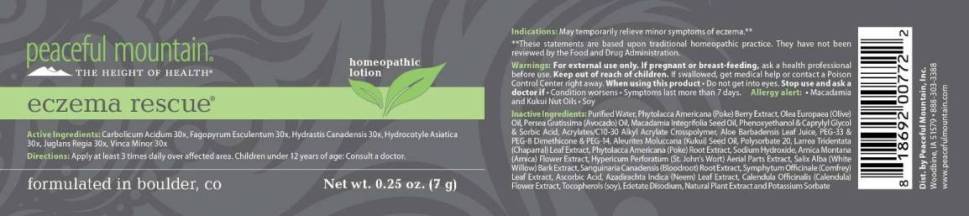 DRUG LABEL: Eczema Rescue
NDC: 43846-0017 | Form: LOTION
Manufacturer: Peaceful Mountain, Inc.
Category: homeopathic | Type: HUMAN OTC DRUG LABEL
Date: 20250521

ACTIVE INGREDIENTS: PHENOL 30 [hp_X]/1 g; FAGOPYRUM ESCULENTUM 30 [hp_X]/1 g; GOLDENSEAL 30 [hp_X]/1 g; CENTELLA ASIATICA 30 [hp_X]/1 g; JUGLANS REGIA LEAF 30 [hp_X]/1 g; JUGLANS REGIA FRUIT RIND, IMMATURE 30 [hp_X]/1 g; VINCA MINOR 30 [hp_X]/1 g
INACTIVE INGREDIENTS: WATER; PHYTOLACCA AMERICANA FRUIT; OLIVE OIL; AVOCADO OIL; MACADAMIA OIL; PHENOXYETHANOL; CAPRYLYL GLYCOL; SORBIC ACID; CARBOMER INTERPOLYMER TYPE A (ALLYL SUCROSE CROSSLINKED); ALOE VERA LEAF; POLYETHYLENE GLYCOL 1500; PEG-8 DIMETHICONE; POLYETHYLENE GLYCOL 700; KUKUI NUT OIL; POLYSORBATE 20; LARREA TRIDENTATA LEAF; PHYTOLACCA AMERICANA ROOT; SODIUM HYDROXIDE; ARNICA MONTANA FLOWER; ST. JOHN'S WORT; SALIX ALBA BARK; SANGUINARIA CANADENSIS ROOT; COMFREY LEAF; ASCORBIC ACID; AZADIRACHTA INDICA LEAF; CALENDULA OFFICINALIS FLOWER; .ALPHA.-TOCOPHEROL; EDETATE DISODIUM; ORIGANUM VULGARE SUBSP. HIRTUM FLOWER; POTASSIUM SORBATE

Drug Facts:

ACTIVE INGREDIENTS:

Carbolicum Acidum 30X, Fagopyrum Esculentum 30X, Hydrastis Canadensis 30X, Hydrocotyle Asiatica 30X, Juglans Regia 30X, Vinca Minor 30X

INDICATIONS:

May temporarily relieve minor symptoms of eczema.**

** These statements are based upon traditional homeopathic practice. They have not been reviewed by the Food and Drug Administration.

WARNINGS:

For external use only.

If pregnant or breast-feeding, ask a health professional before use.

Keep out of reach of children. If swallowed, get medical help or contact a Poison Control Center right away.

When using this product: Do not get into eyes.

Stop use and ask a doctor if: Condition worsens. Symptoms last more than 7 days.

ALLERGY ALERT: Macadamia and Kukui Nut Oils, Soy

DIRECTIONS:

Apply at least 3 times daily over the affected area.

Children under 12 years of age: Consult a doctor

INACTIVE INGREDIENTS:

Purified Water, Poke (Berry) Phytolacca Americana, Olive Oil (Olea Europaea), Avocado Oil (Persea Gratissima), Macadamia Nut Oil (Macadamia Integrifolia), Phenoxyethanol, Caprylyl Glycol, Sorbic Acid, Acrylates/C10 Alkyl Acrylate Crosspolymer, Aloe Barbadensis Leaf Juice, PEG-33, PEG 8 DIMETHICONE, PEG-14, Kukui Nut Oil (Aleurites Moluccana), Polysorbate 20, Chaparral Leaf (Larrea Tridentata), Poke Root (Phytolacca Americana), Arnica Montana Flower, St. Johns Wort Aerial Parts (Hypericum Perforatum), White Willow Bark (Salix Alba), Bloodroot Root (Sanguinaria Canadensis), Comfrey Leaf (Symphytum Officinale), Ascorbic Acid, Neem Leaf (Azadirachta Indica), Calendula Officinalis Flower, Vitamin E Oil, Edetate Disodium (EDTA), Oregano, Potassium Sorbate

Keep out of reach of children. If swallowed, get medical help or contact a Poison Control Center right away.

INDICATIONS:

May temporarily relieve minor symptoms of eczema.**

** These statements are based upon traditional homeopathic practice. They have not been reviewed by the Food and Drug Administration.

QUESTIONS

Dist by:

Peaceful Mountain, Inc.

Woodbine, IA 51579 883-303-3388

www.peacefulmountain.com

PACKAGE LABEL DISPLAY:

peaceful mountain
THE HEIGHT OF HEALTH

eczema rescue

homeopathic lotion

formulated in boulder, co
Net wt. 0.25 oz, (7 g)